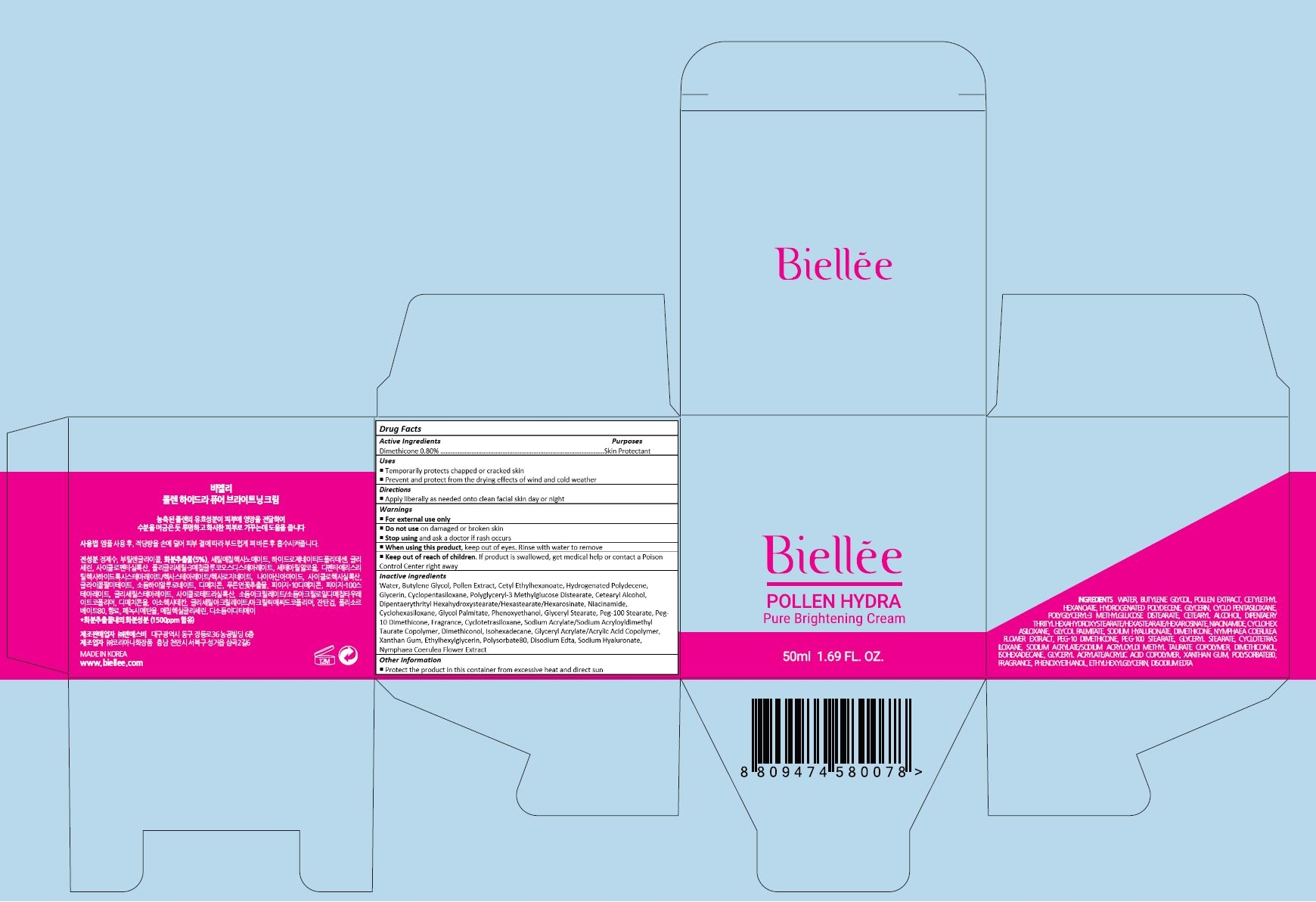 DRUG LABEL: Biellee Pollen Hydra Pure Brightening Cream
NDC: 70784-004 | Form: CREAM
Manufacturer: NSB CO., LTD.
Category: otc | Type: HUMAN OTC DRUG LABEL
Date: 20160621

ACTIVE INGREDIENTS: DIMETHICONE 0.4 mg/50 mL
INACTIVE INGREDIENTS: WATER; BUTYLENE GLYCOL; BEE POLLEN; CETYL ETHYLHEXANOATE; HYDROGENATED POLYDECENE (550 MW); GLYCERIN; CYCLOMETHICONE 5; CETOSTEARYL ALCOHOL; NIACINAMIDE; CYCLOMETHICONE 6; GLYCOL PALMITATE; PHENOXYETHANOL; GLYCERYL MONOSTEARATE; PEG-100 STEARATE; PEG-10 DIMETHICONE (600 CST); CYCLOMETHICONE 4; SODIUM ACRYLATE/SODIUM ACRYLOYLDIMETHYLTAURATE COPOLYMER (4000000 MW); DIMETHICONOL (2000 CST); ISOHEXADECANE; XANTHAN GUM; ETHYLHEXYLGLYCERIN; POLYSORBATE 80; EDETATE DISODIUM; HYALURONATE SODIUM; NYMPHAEA CAERULEA FLOWER

Drug Facts

ACTIVE INGREDIENT

DIMETHICONE 0.80%

PURPOSE

Skin Protectant

INDICATIONS AND USAGE

Temporarily protects chapped or cracked skin
Prevent and protect from the drying effects of wind and cold weather

DOSAGE AND ADMINISTRATION

Apply liberally as needed onto clean facial skin day or night

WARNINGS

For external use only

Do not use on damaged or broken skin

When using this product, keep out of eyes. Rinse with water to remove.

Stop using and ask a doctor if rash occurs.

KEEP OUT OF REACH OF CHILDREN

Keep out of reach of the children. If product is swallowed, get medical help or contact a poison control center right away.

INACTIVE INGREDIENT

WATER
BUTYLENE GLYCOL
POLLEN EXTRACT
CETYL ETHYLHEXANOATE
HYDROGENATED POLYDECENE
GLYCERIN
CYCLOPENTASILOXANE
POLYGLYCERYL-3 METHYLGLUCOSE DISTEARATE
CETEARYL ALCOHOL
DIPENTAERYTHRITYL HEXAHYDROXYSTEARATE/HEXASTEARATE/HEXAROSINATE
NIACINAMIDE
CYCLOHEXASILOXANE
GLYCOL PALMITATE
PHENOXYETHANOL
GLYCERYL STEARATE
PEG-100 STEARATE
PEG-10 DIMETHICONE
FRAGRANCE
CYCLOTETRASILOXANE
SODIUM ACRYLATE/SODIUM ACRYLOYLDIMETHYL TAURATE COPOLYMER
DIMETHICONOL
ISOHEXADECANE
GLYCERYL ACRYLATE/ACRYLIC ACID COPOLYMER
XANTHAN GUM
ETHYLHEXYLGLYCERIN
POLYSORBATE80
DISODIUM EDTA
SODIUM HYALURONATE
NYMPHAEA COERULEA FLOWER EXTRACT